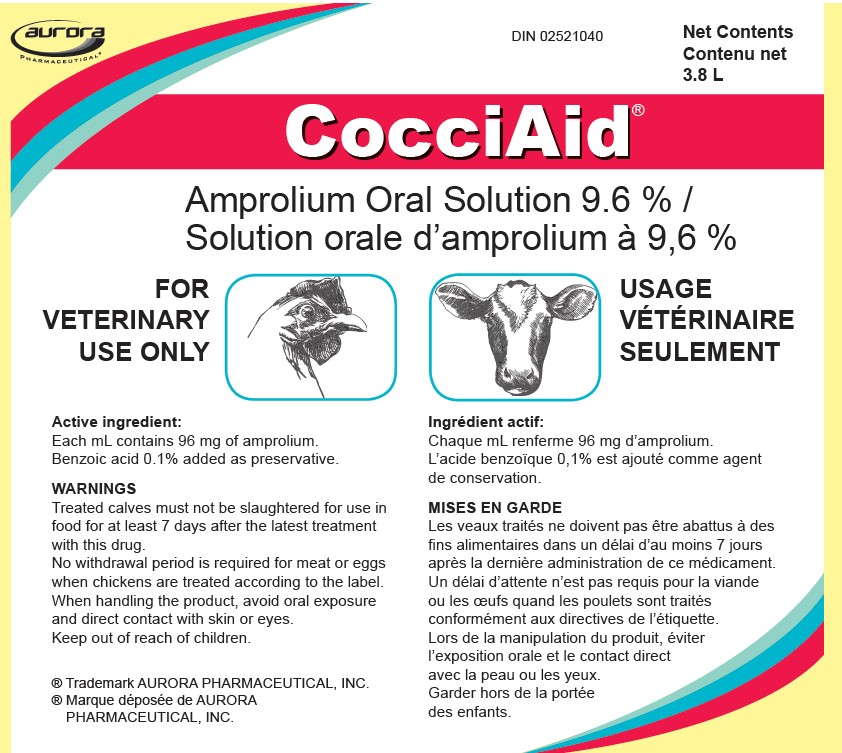 DRUG LABEL: CocciAid
NDC: 51072-111 | Form: SOLUTION
Manufacturer: Aurora Pharmaceutical, Inc.
Category: animal | Type: OTC ANIMAL DRUG LABEL
Date: 20230301

ACTIVE INGREDIENTS: AMPROLIUM 96 mg/1 mL
INACTIVE INGREDIENTS: WATER

CocciAid®

(amprolium)

9.6% Oral Solution

DIN 02521040

Net Contents:

3.8 L

FOR VETERINARY USE ONLY

Active Ingredient:

Each mL contains 96 mg of amprolium.

Benzoic acid 0.1% added as preservative.

INDICATIONS:

CHICKENS
As an aid in the treatment of caecal coccidiosis in growing chickens and laying birds.
CALVES
As an aid in the treatment of coccidiosis caused by Eimeria bovis and E. zuernii in calves.

USE DIRECTIONS:

CHICKENS
As soon as caecal coccidiosis is diagnosed, give 0.024% amprolium in the drinking water for 5 to 7 days.
Continue treatment with 0.006% amprolium medicated water for an additional one to two weeks.
No other source of drinking water should be available to the birds during this time.
Use as the sole source of amprolium.

CALVES
0.012% amprolium in drinking water for 5 days. At the usual rate of water consumption, this will provide a daily intake of approximately 10 mg of amprolium per kg of body weight. Give as the sole source of water during the treatment period.

NOTE
When one or more calves show signs of coccidiosis, it is likely that the rest of the group have been exposed, and all calves in the group should be treated.

WARNING:

Treated calves must not be slaughtered for use in food for at least 7 days after the latest treatment with this drug.
No withdrawal period is required for meat or eggs when chickens are treated according to the label.
When handling the product, avoid oral exposure and direct contact with skin or eyes.
Keep out of reach of children.

CAUTIONS:

CHICKENS
If no improvement is noted within 3 days, have the diagnosis reconfirmed and follow the instructions of your veterinarian or poultry pathologist. Losses may result from intercurrent disease or other conditions affecting drug intake which can contribute to the virulence of coccidiosis under field conditions.

CALVES
For an appropriate diagnosis, a microscopic examination of the feces should be done before treatment. When treating outbreaks, drug should be administered promptly after diagnosis is determined.
Do not use in calves intended for future breeding

MIXING DIRECTIONS:

To prepare 200 L of medicated water

DOSAGE | MIXING DIRECTIONS
0.024% | Add 500 mL of CocciAid® (amprolium) 9.6% Solution to about 25 L of water in a 200 L medication barrel. Stir, then add water to the 200 L mark. Stir thoroughly.
0.012% | Follow same directions as above but use 250 mL of CocciAid® 9.6% Solution.
0.006% | Follow same directions as above but use 125 mL of CocciAid® 9.6% Solution.

STORAGE:

Store at 15° to 25°C. Protect from freezing.

REORDER NO: 24003

Manufactured by:

Aurora Pharmaceutical, Inc.
Northfield, MN 55057
1-888-215-1256

Distributed by:

Partnar Animal Health Inc.

Ilderton, Ontario NDM 2A0

IN 50-1628 09/2021

Container Label

PRINCIPAL DISPLAY PANEL - 3.8L bottle label